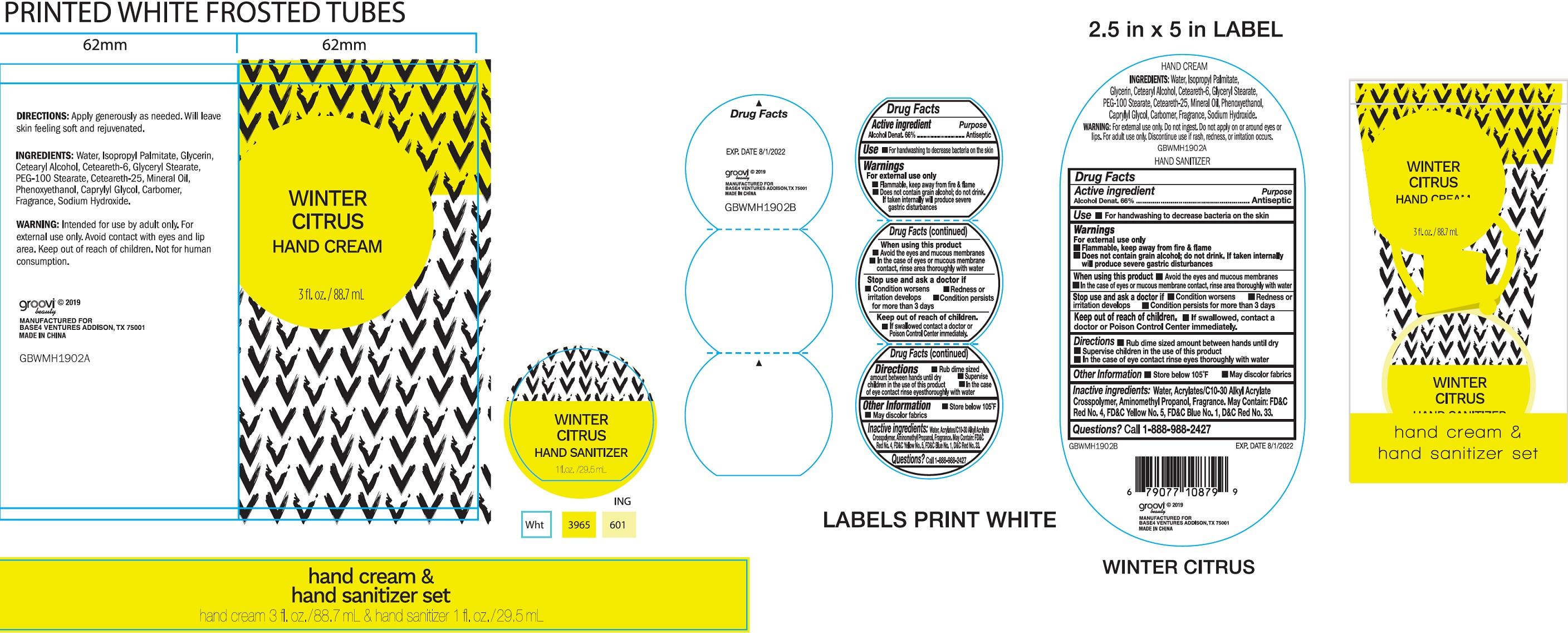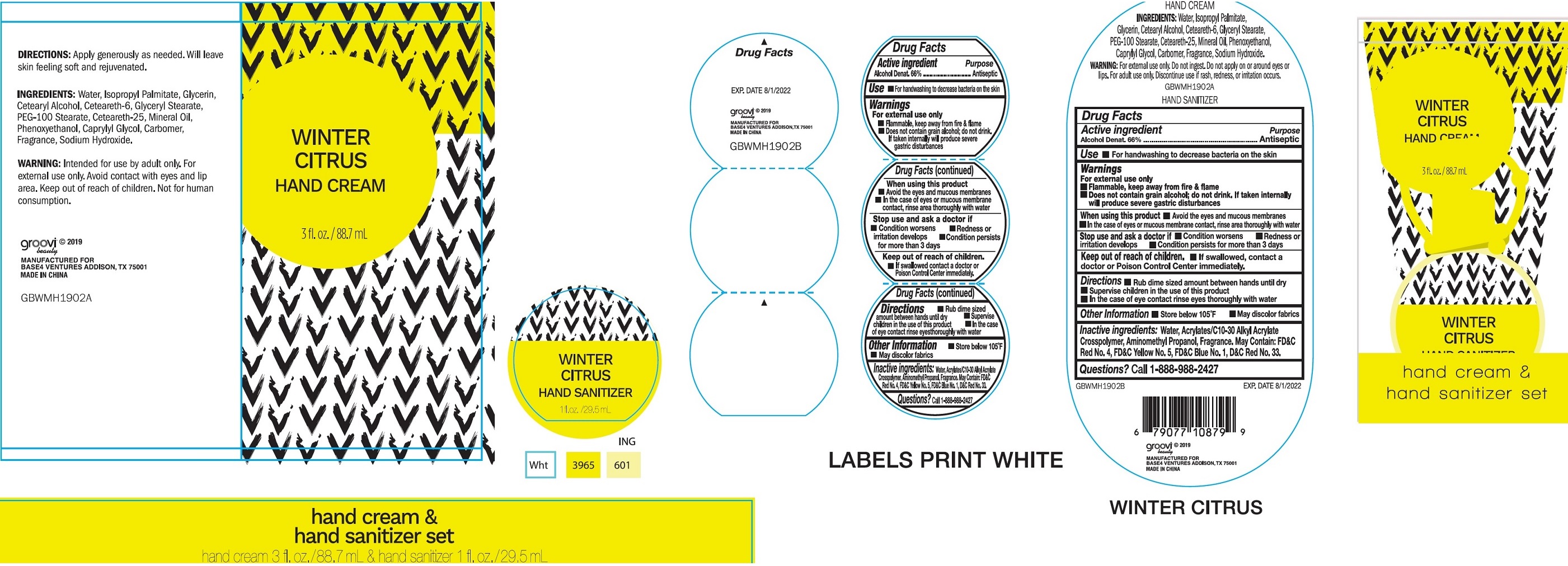 DRUG LABEL: Hand Care Set Winter Citrus
NDC: 62651-022 | Form: KIT | Route: TOPICAL
Manufacturer: Base4 Ventures, LLC
Category: otc | Type: HUMAN OTC DRUG LABEL
Date: 20190626

ACTIVE INGREDIENTS: ALCOHOL 660 mL/1 mL
INACTIVE INGREDIENTS: WATER; AMINOMETHYLPROPANOL; FD&C RED NO. 4; FD&C YELLOW NO. 5; FD&C BLUE NO. 1; D&C RED NO. 33

Hand Care Set Winter Citrus

Active ingredient

Alcohol Denat. 66%

Purpose

Antiseptic

Use

- For handwashing to decrease bacteria on the skin

Warnings

For external use only

- Flammable. Keep away from fire & flame
- Does not contain grain alcohol; do not drink. If taken internally will produce severe gastric disturbances

When using this product

- Avoid the eyes and mucous membranes
- In the case of eyes or mucous membrane contact, rinse area thoroughly with water

Stop use and ask a doctor if

- Condition worsens
- Redness or irritation develops
- Condition persist for more than 3 days

Keep out of reach of children.

If swallowed, contact a doctor or Poison Control Center immediately.

Directions

- Rub dime sized amount between hands until dry
- Supervise children in the use of this product
- In the case of eye contact rinse eyes thoroughly with water

Other information

- Store below 105°F
- May discolor fabrics

Inactive ingredients:

Water, Acrylates/C10-30 Alkyl Acrylate Crosspolymer, Aminomethyl Propanol, Fragrance. May Contain: FD&C Red No.4, FD&C Yellow No.5, FD&C Blue No.1, D&C Red No.33.

Questions?

Call 1-888-988-2427